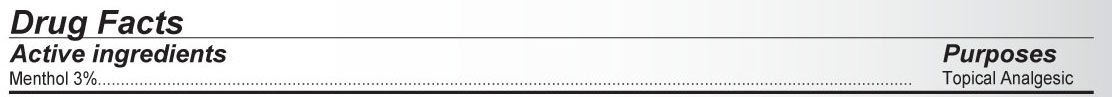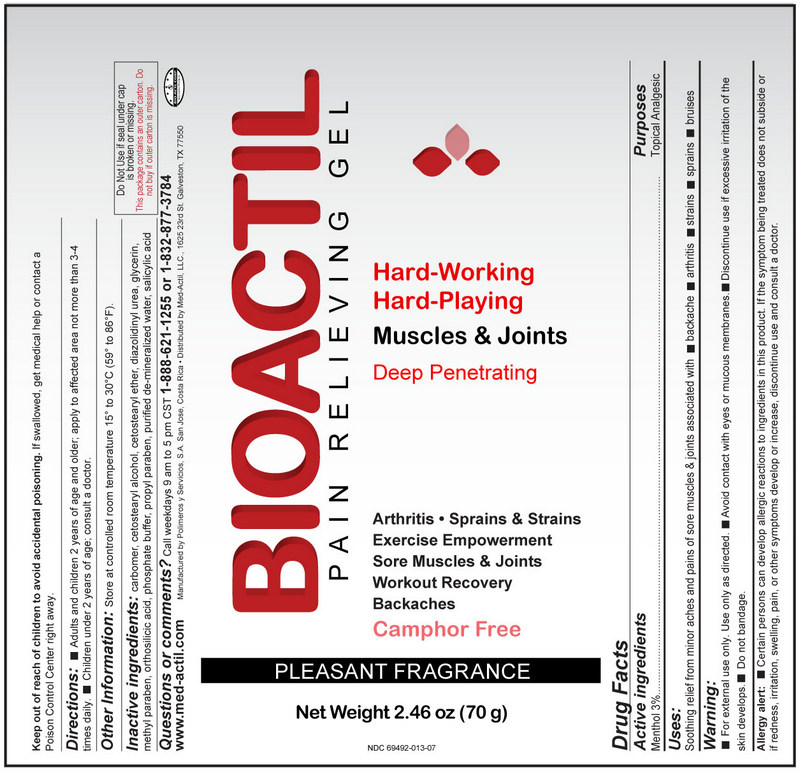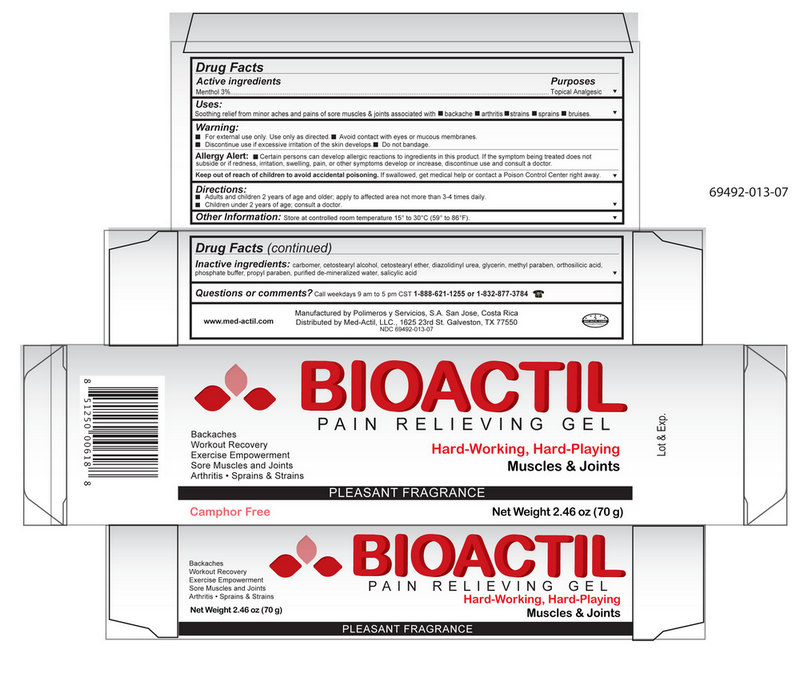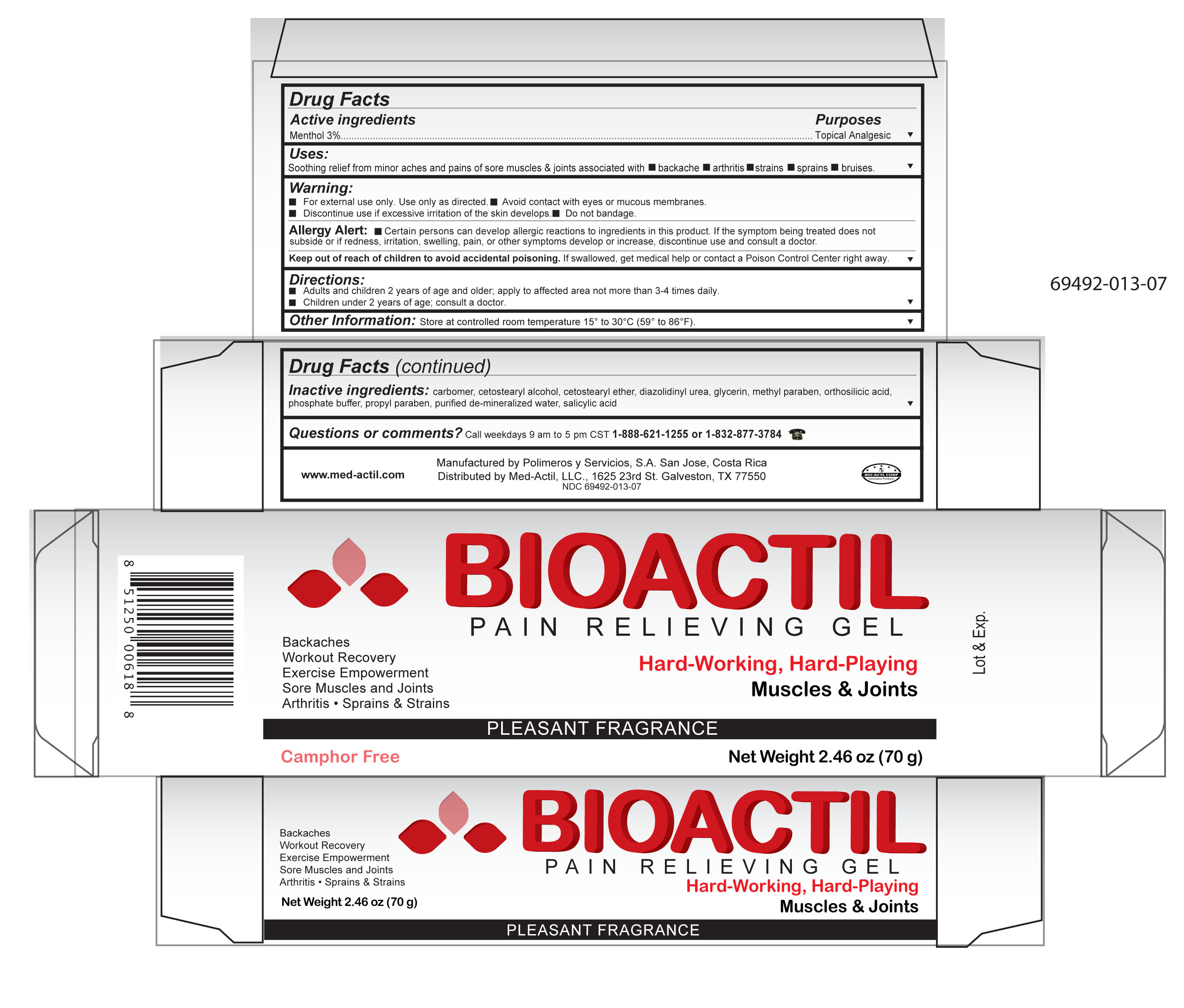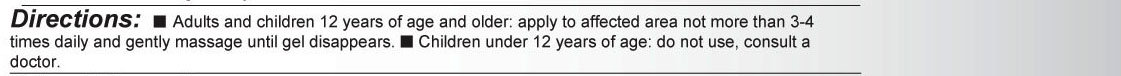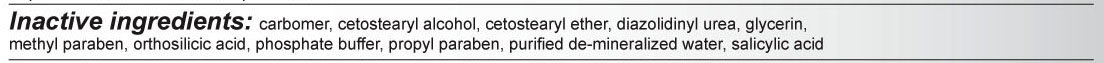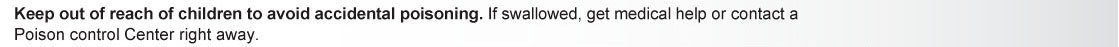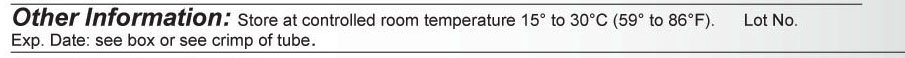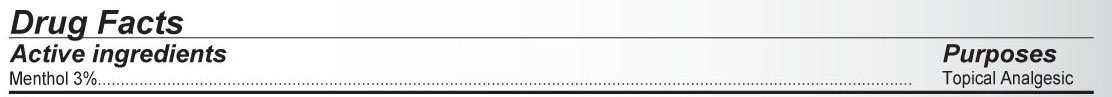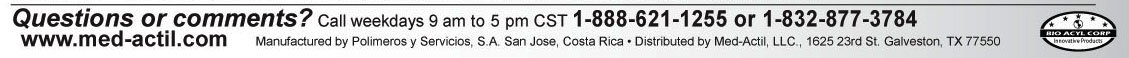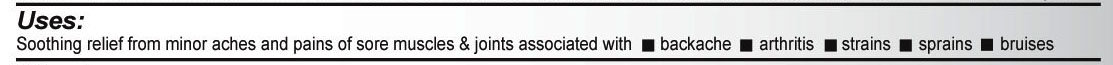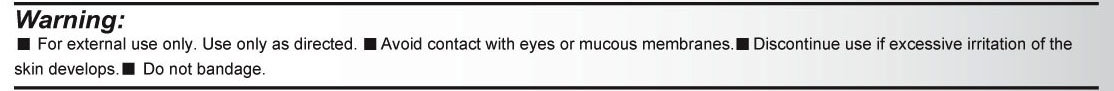 DRUG LABEL: BIOACTIL
NDC: 69492-013 | Form: GEL
Manufacturer: POLIMEROS Y SERVICIOS S.A.
Category: otc | Type: HUMAN OTC DRUG LABEL
Date: 20190313

ACTIVE INGREDIENTS: MENTHOL 30 mg/1 g
INACTIVE INGREDIENTS: ALLANTOIN; CARBOMER 940; CETOSTEARYL ALCOHOL; POLYOXYL 20 CETOSTEARYL ETHER; DIAZOLIDINYL UREA; METHYLPARABEN; ORTHOSILICIC ACID; SODIUM PHOSPHATE, DIBASIC; PROPYLPARABEN; SALICYLIC ACID; WATER

Submission for Bioactil Pain Relieving Gel

Detail showing Active Ingredient from package

Activeingredient.jpg

Information shown both on container label and paclage

Detail showing Inactive ingredient from package

Inactiveingredients.jpg

Information shown both on container label and paclage

Detail showing Purpose within Active Ingredients from package

Purpose.jpg

nformation shown both on container label and package

Detail showing Instructions for use and named Uses from package

Uses.jpg

Information shown both on container label and package

Detail showing Dosage and Administration within Directions from package

Directions.jpg

Information shown both on container lable and package

Detail showing Warnings from package

Warning.jpg

Information shown both on container label and package

Detail showing Keep Out of Reach of Children within Warnings from package

KeepoutofreachofchildrenBioactil.jpg

Information shown on package and container label

Detail showing Questions from package

Questionsorcomments.jpg

nformation shown both on container label and package

Detail showing Other Information from package

OtherInformation.jpg

Information shown both on container label and package

Representative sample image of carton/container label

General view of inner container label

Bioactil 6 frente.jpg

Bioactilfrente.jpg

General view of box content of labeling

Bioactilbox.jpg

Bioactil box.jpg